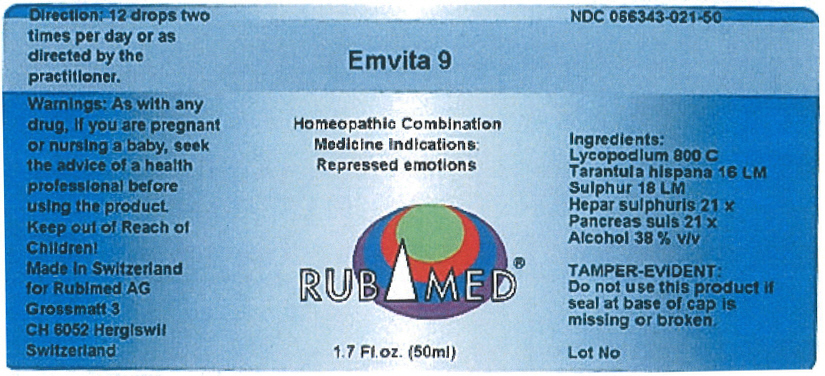 DRUG LABEL: Emvita 9
NDC: 66343-021 | Form: LIQUID
Manufacturer: RUBIMED AG
Category: otc | Type: HUMAN OTC DRUG LABEL
Date: 20150708

ACTIVE INGREDIENTS: LYCOPODIUM CLAVATUM SPORE 800 [hp_C]/1 mL; LYCOSA TARANTULA 16 [hp_M]/1 mL; SULFUR 18 [hp_M]/1 mL; CALCIUM SULFIDE 21 [hp_X]/1 mL; SUS SCROFA PANCREAS 21 [hp_X]/1 mL
INACTIVE INGREDIENTS: ALCOHOL 0.4 mL/1 mL

Emvita 9

INDICATIONS AND USAGE

PURPOSE

Homeopathic Combination Medicine Indications: Repressed emotions

Ingredients

INACTIVE INGREDIENT

Lycopodium 800 C
Tarantula hispana 16 LM
Sulphur 18 LM
Hepar sulphuris 21 x
Pancreas suis 2l x
Alcohol 38 % v/v

TAMPER-EVIDENT

Do not use this product if seal at base of cap is missing or broken.

Direction

12 drops two times per day or as directed by the practitioner.

Warnings

PREGNANCY OR BREAST FEEDING

As with any drug, if you are pregnant or nursing a baby, seek the advice of a health professional before using the product.

Keep out of Reach of Children!

PRINCIPAL DISPLAY PANEL - 50 ml Bottle Label

Emvita 9

Homeopathic Combination
Medicine Indications:
Repressed emotions

RUBIMED®

1.7 Fl.oz. (50ml)